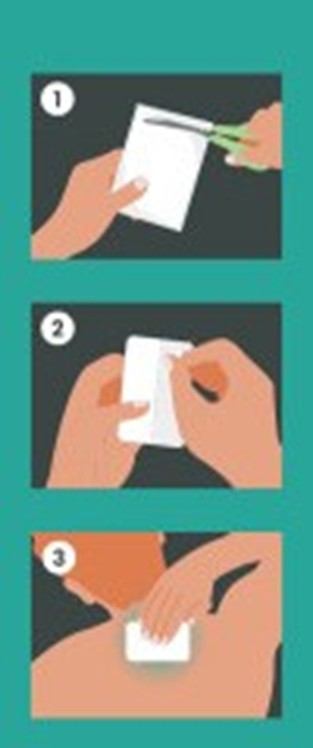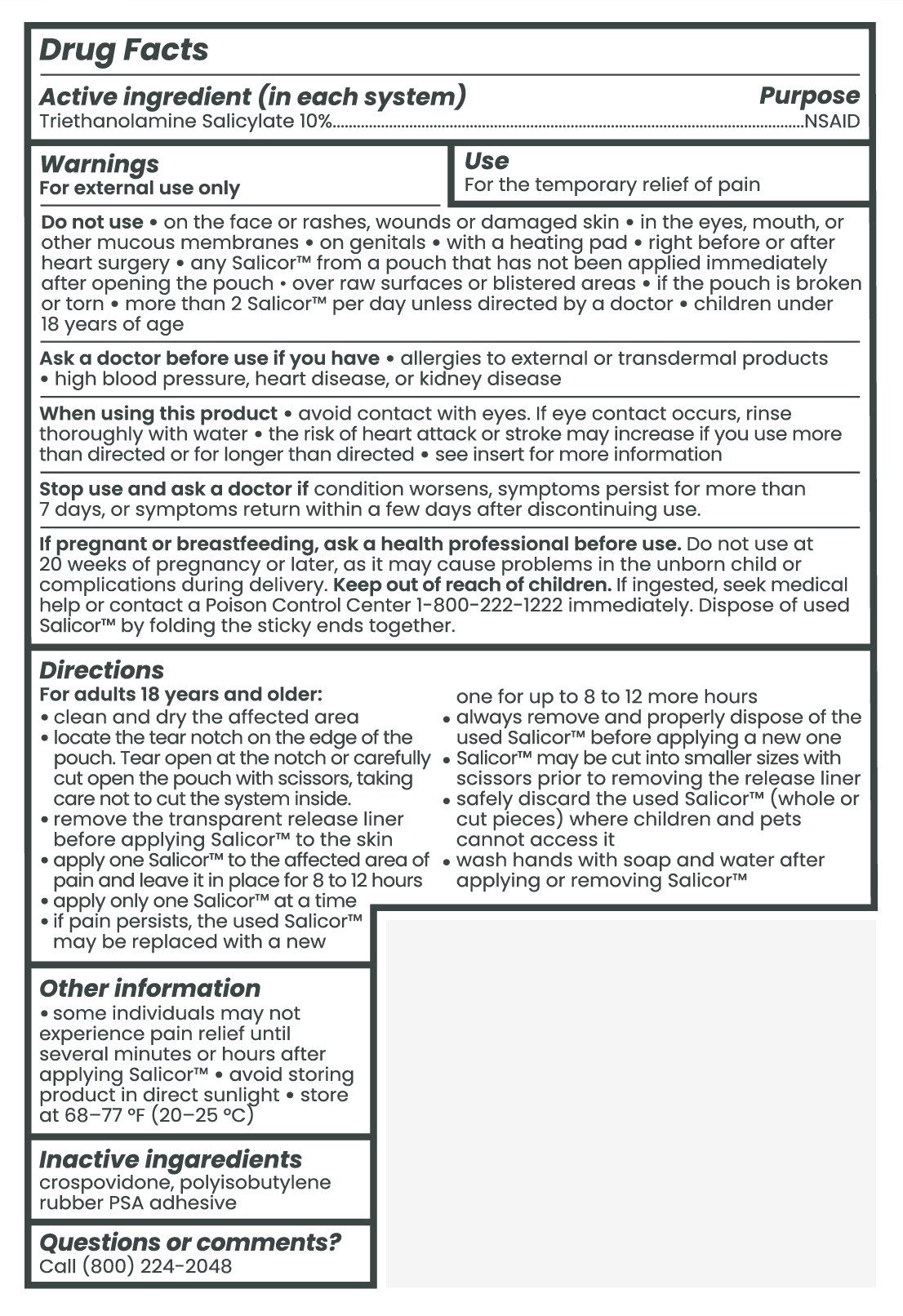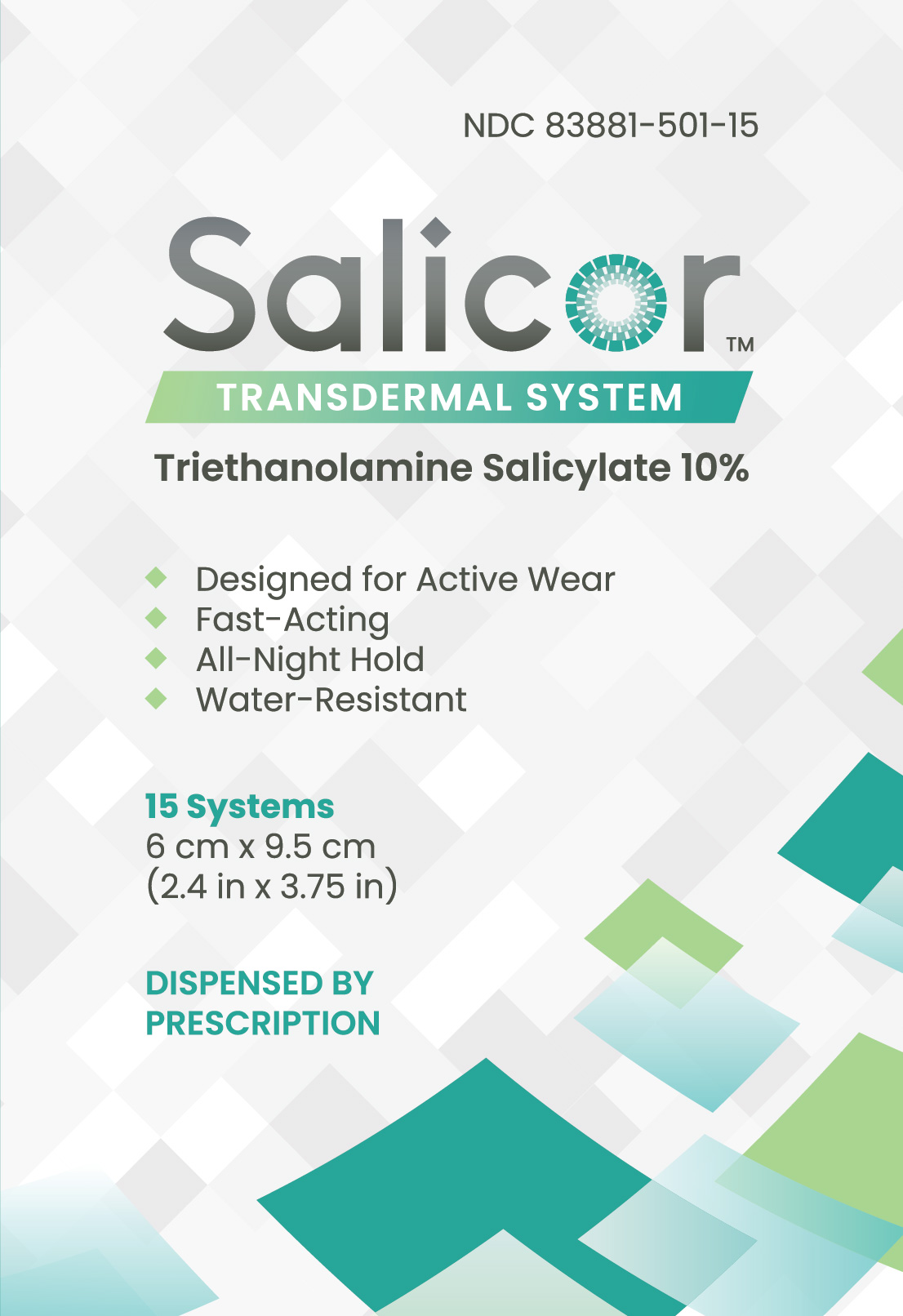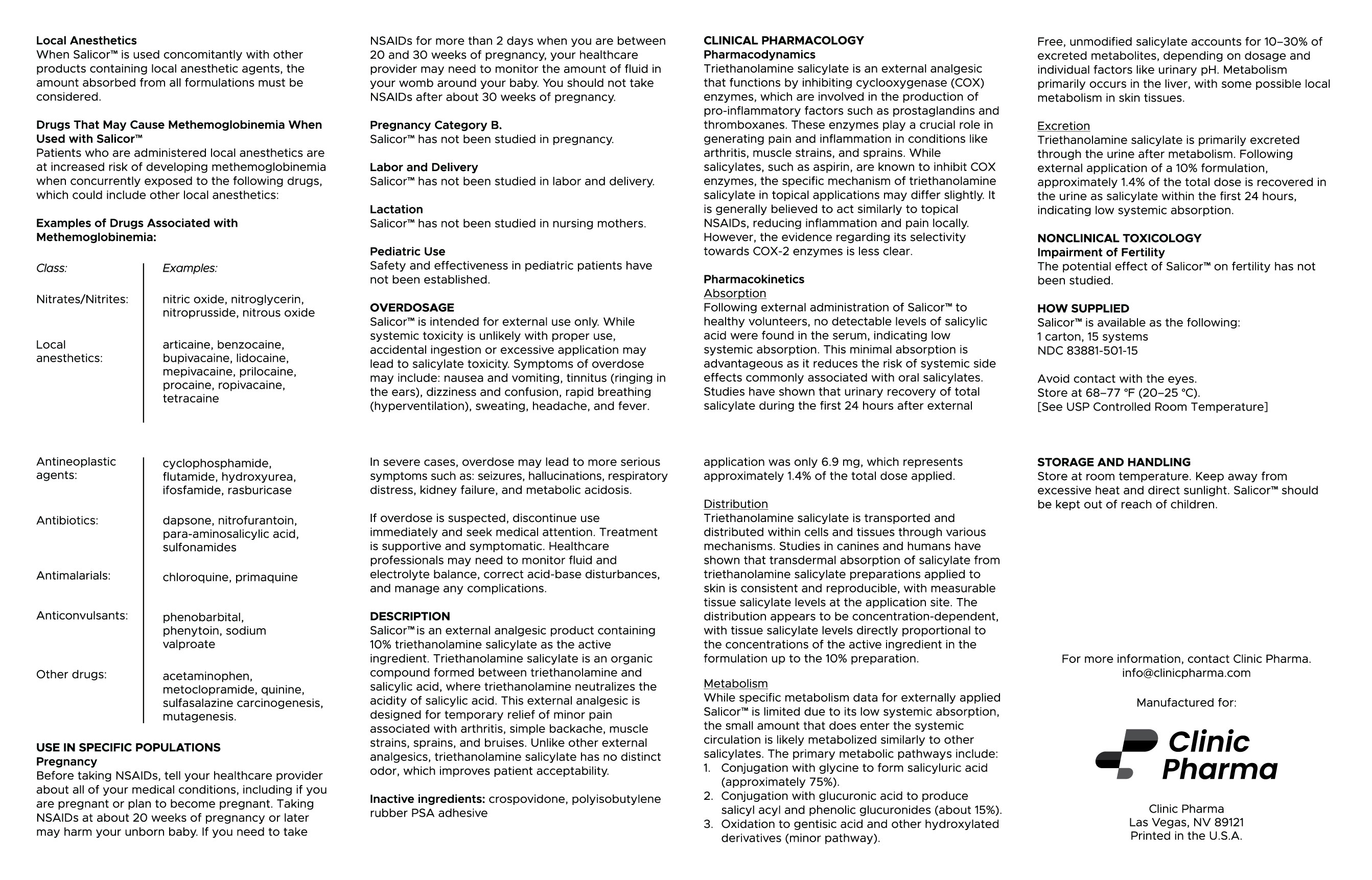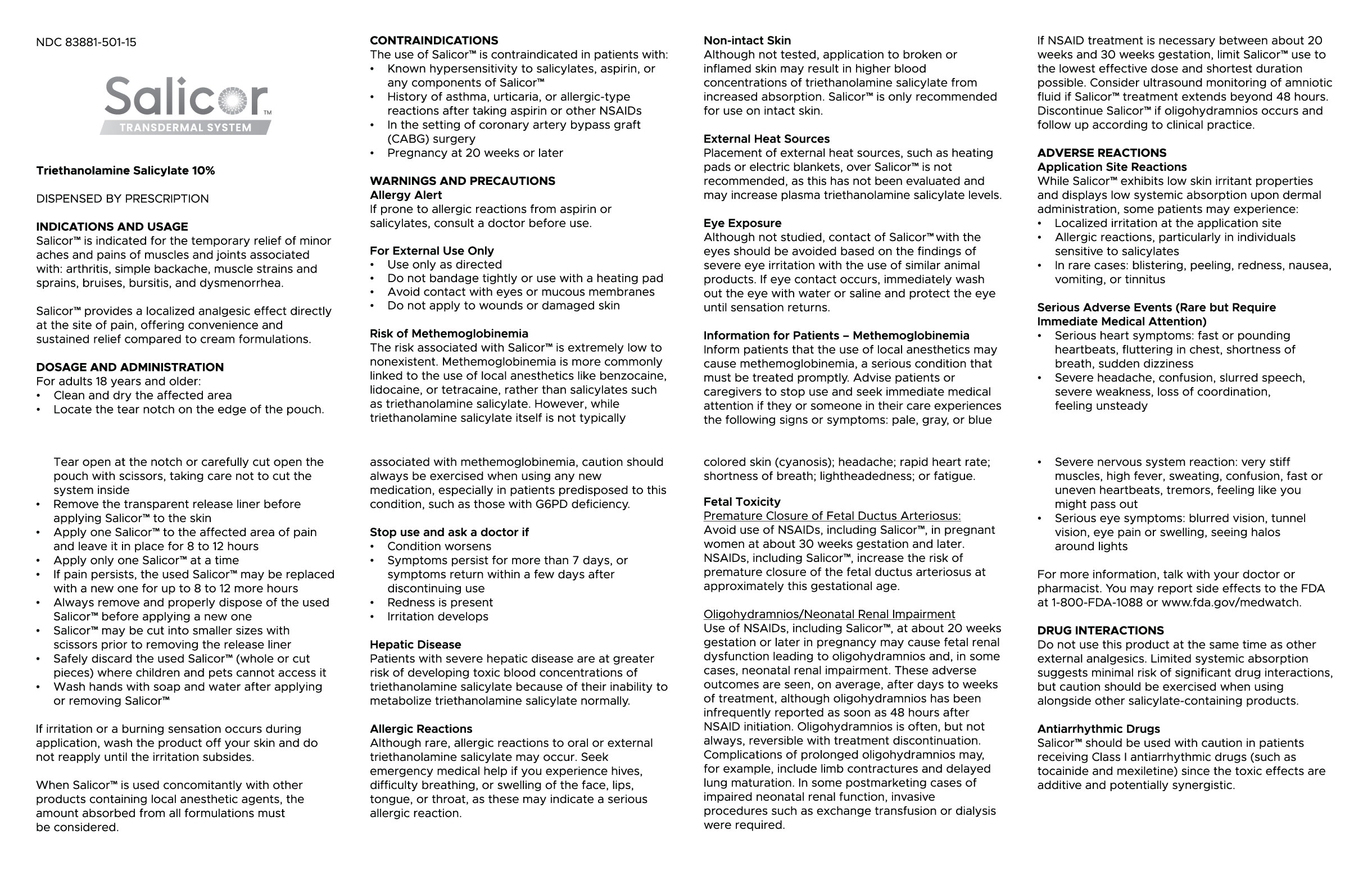 DRUG LABEL: Salicor
NDC: 83881-501 | Form: PATCH
Manufacturer: Clinic Pharma
Category: prescription | Type: HUMAN PRESCRIPTION DRUG LABEL
Date: 20251022

ACTIVE INGREDIENTS: TEA-SALICYLATE 40.2 mg/1 1
INACTIVE INGREDIENTS: 2-ETHYLHEXYL ACRYLATE-METHYL ACRYLATE-GLYCIDYL METHACRYLATE-ACRYLIC ACID COPOLYMER (FOR DURO-TAK 387-2353); HEPTANE; KOLLIDON SR; ISOPROPYL ALCOHOL

SALICOR (triethanolamine salicylate patch)

DESCRIPTION

Salicor™ is an external analgesic product containing 10% triethanolamine salicylate as the active ingredient. Triethanolamine salicylate is an organic compound formed between triethanolamine and salicylic acid, where triethanolamine neutralizes the acidity of salicylic acid. This external analgesic is designed for temporary relief of minor pain associated with arthritis, simple backache, muscle strains, sprains, and bruises. Unlike other external analgesics, triethanolamine salicylate has no distinct odor, which improves patient acceptability.

HOW SUPPLIED

Salicor™ is available as the following:
1 carton, 15 systems
NDC 83881-501-15

DOSAGE AND ADMINISTRATION

For adults 18 years and older:
• Clean and dry the affected area
• Locate the tear notch on the edge of the pouch. Tear open at the notch or carefully cut open the pouch with scissors, taking care not to cut the system inside
• Remove the transparent release liner before applying Salicor™ to the skin
• Apply one Salicor™ to the affected area of pain and leave it in place for 8 to 12 hours
• Apply only one Salicor™ at a time
• If pain persists, the used Salicor™ may be replaced with a new one for up to 8 to 12 more hours
• Always remove and properly dispose of the used Salicor™ before applying a new one
• Salicor™ may be cut into smaller sizes with scissors prior to removing the release liner
• Safely discard the used Salicor™ (whole or cut pieces) where children and pets cannot access it
• Wash hands with soap and water after applying or removing Salicor™

Visual Guide provided below:

These highlights do not include all the information needed to use Salicor™ safely and effectively. See full prescribing information for Salicor™

STORAGE AND HANDLING

Avoid contact with the eyes. Keep away from excessive heat and direct sunlight. Salicor™ should be kept out of reach of children.
Store at 20° to 25°C (68° to 77°F).
[See USP Controlled Room Temperature]

Pharmacodynamics

Triethanolamine salicylate is an external analgesic that functions by inhibiting cyclooxygenase (COX) enzymes, which are involved in the production of pro-inflammatory factors such as prostaglandins and thromboxanes. These enzymes play a crucial role in generating pain and inflammation in conditions like arthritis, muscle strains, and sprains. While salicylates, such as aspirin, are known to inhibit COX enzymes, the specific mechanism of triethanolamine salicylate in topical applications may differ slightly. It is generally believed to act similarly to topical NSAIDs, reducing inflammation and pain locally. However, the evidence regarding its selectivity towards COX-2 enzymes is less clear.

Drugs That May Cause Methemoglobinemia When Used with Salicor™

Patients who are administered local anesthetics are at increased risk of developing methemoglobinemia when concurrently exposed to the following drugs, which could include other local anesthetics:

Examples of Drugs Associated with Methemoglobinemia
Class: Nitrates/Nitrites: Local anesthetics: Antineoplastic agents: Antibiotics: Antimalarials: Anticonvulsants: Other drugs: Examples: nitric oxide, nitroglycerin, nitroprusside, nitrous oxide articaine, benzocaine, bupivacaine, lidocaine, mepivacaine, prilocaine, procaine, ropivacaine, tetracaine cyclophosphamide, flutamide, hydroxyurea, ifosfamide, rasburicase dapsone, nitrofurantoin, para-aminosalicylic acid, sulfonamides chloroquine, primaquine phenobarbital, phenytoin, sodium valproate acetaminophen, metoclopramide, quinine, sulfasalazine carcinogenesis, mutagenesis

Pharmacokinetics

Absorption
Following external administration of Salicor™ to healthy volunteers, no detectable levels of salicylic acid were found in the serum, indicating low systemic absorption. This minimal absorption is advantageous as it reduces the risk of systemic side effects commonly associated with oral salicylates. Studies have shown that urinary recovery of total salicylate during the first 24 hours after external application was only 6.9 mg, which represents approximately 1.4% of the total dose applied.

Distribution
Triethanolamine salicylate is transported and distributed within cells and tissues through various mechanisms. Studies in canines and humans have shown that transdermal absorption of salicylate from triethanolamine salicylate preparations applied to skin is consistent and reproducible, with measurable tissue salicylate levels at the application site. The distribution appears to be concentration-dependent, with tissue salicylate levels directly proportional to the concentrations of the active ingredient in the formulation up to the 10% preparation.

Metabolism
While specific metabolism data for externally applied Salicor™ is limited due to its low systemic absorption, the small amount that does enter the systemic circulation is likely metabolized similarly to other salicylates. The primary metabolic pathways include:
1. Conjugation with glycine to form salicyluric acid (approximately 75%).
2. Conjugation with glucuronic acid to produce salicyl acyl and phenolic glucuronides (about 15%).
3. Oxidation to gentisic acid and other hydroxylated derivatives (minor pathway).
Free, unmodified salicylate accounts for 10–30% of excreted metabolites, depending on dosage and individual factors like urinary pH. Metabolism primarily occurs in the liver, with some possible local metabolism in skin tissues.

Excretion
Triethanolamine salicylate is primarily excreted through the urine after metabolism. Following external application of a 10% formulation, approximately 1.4% of the total dose is recovered in the urine as salicylate within the first 24 hours, indicating low systemic absorption.

INDICATION AND USAGE

Salicor™ is indicated for the temporary relief of minor aches and pains of muscles and joints associated with: arthritis, simple backache, muscle strains and sprains, bruises, bursitis, and dysmenorrhea.
Salicor™ provides a localized analgesic effect directly at the site of pain, offering convenience and sustained relief compared to cream formulations.

PRECAUTIONS

General

If irritation or a burning sensation occurs during application, wash the product off your skin and do not reapply until the irritation subsides.
When Salicor™ is used concomitantly with other products containing local anesthetic agents, the amount absorbed from all formulations must be considered.

Stop use and ask a doctor if
• Condition worsens
• Symptoms persist for more than 7 days, or symptoms return within a few days after discontinuing use
• Redness is present
• Irritation develops

Hepatic Disease
Patients with severe hepatic disease are at greater risk of developing toxic blood concentrations of triethanolamine salicylate because of their inability to metabolize triethanolamine salicylate normally.

Allergic Reactions
Although rare, allergic reactions to oral or external triethanolamine salicylate may occur. Seek emergency medical help if you experience hives, difficulty breathing, or swelling of the face, lips, tongue, or throat, as these may indicate a serious allergic reaction.

Non-intact Skin
Although not tested, application to broken or inflamed skin may result in higher blood concentrations of triethanolamine salicylate from increased absorption. Salicor™ is only recommended for use on intact skin.

External Heat Sources

Placement of external heat sources, such as heating pads or electric blankets, over Salicor™ is not recommended, as this has not been evaluated and may increase plasma triethanolamine salicylate levels.

Eye Exposure
Although not studied, contact of Salicor™ with the eyes should be avoided based on the findings of severe eye irritation with the use of similar animal products. If eye contact occurs, immediately wash out the eye with water or saline and protect the eye until sensation returns.

Information for Patients Methemoglobinemia
Inform patients that the use of local anesthetics may cause methemoglobinemia, a serious condition that must be treated promptly. Advise patients or caregivers to stop use and seek immediate medical attention if they or someone in their care experiences the following signs or symptoms: pale, gray, or blue colored skin (cyanosis); headache; rapid heart rate; shortness of breath; lightheadedness; or fatigue.

OVERDOSAGE

Salicor™ is intended for external use only. While systemic toxicity is unlikely with proper use, accidental ingestion or excessive application may lead to salicylate toxicity. Symptoms of overdose may include: nausea and vomiting, tinnitus (ringing in the ears), dizziness and confusion, rapid breathing (hyperventilation), sweating, headache, and fever.
In severe cases, overdose may lead to more serious symptoms such as: seizures, hallucinations, respiratory distress, kidney failure, and metabolic acidosis.
If overdose is suspected, discontinue use immediately and seek medical attention. Treatment is supportive and symptomatic. Healthcare professionals may need to monitor fluid and electrolyte balance, correct acid-base disturbances, and manage any complications.

Pregnancy

Before taking NSAIDs, tell your healthcare provider about all of your medical conditions, including if you are pregnant or plan to become pregnant. Taking NSAIDs at about 20 weeks of pregnancy or later may harm your unborn baby. If you need to take NSAIDs for more than 2 days when you are between 20 and 30 weeks of pregnancy, your healthcare provider may need to monitor the amount of fluid in your womb around your baby. You should not take NSAIDs after about 30 weeks of pregnancy.

Pregnancy Category B.
Salicor™ has not been studied in pregnancy.

Labor and Delivery

Salicor™ has not been studied in labor and delivery.

Lactation

Salicor™ has not been studied in nursing mothers.

Pediatric Use

Safety and effectiveness in pediatric patients have not been established.